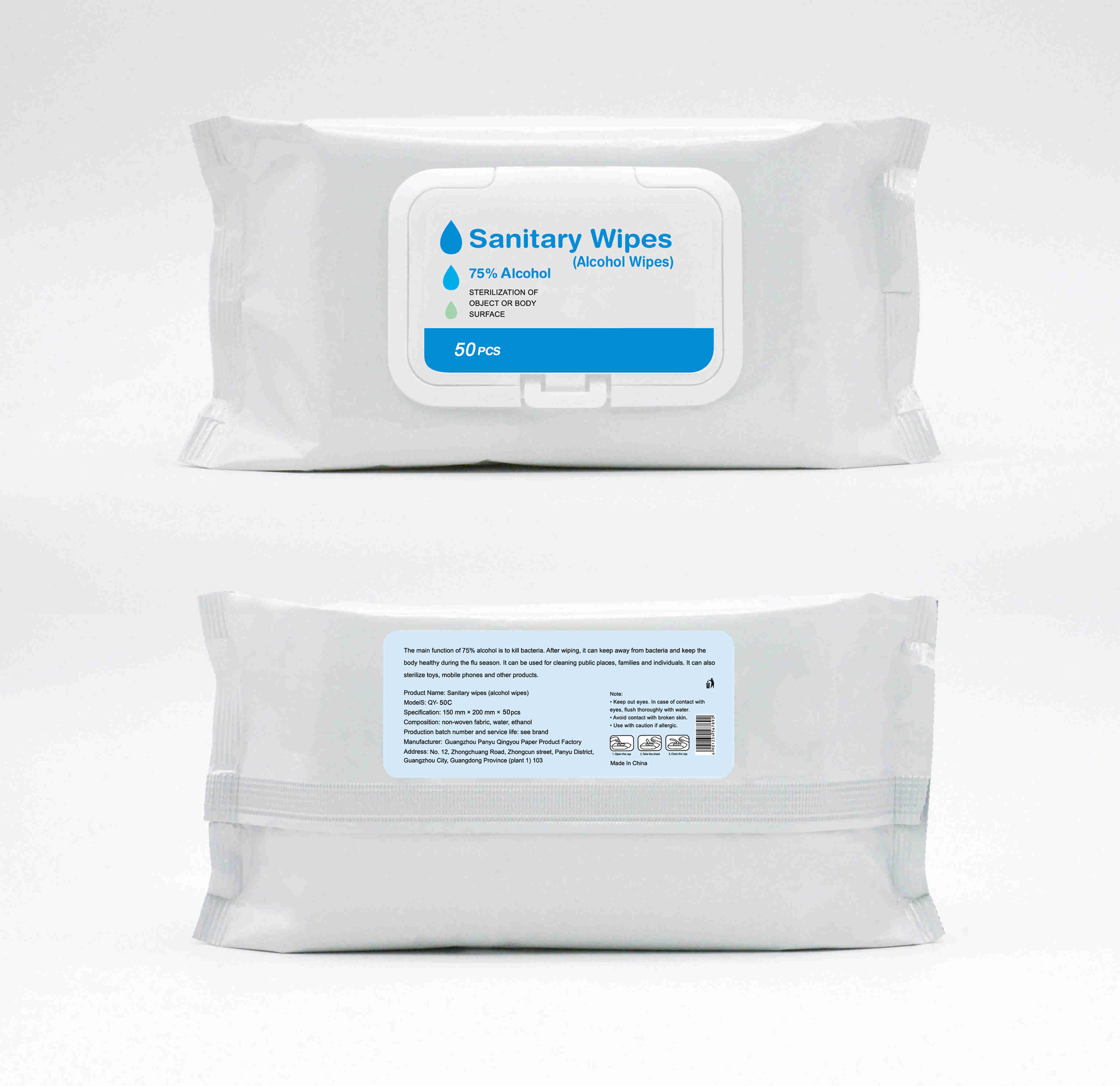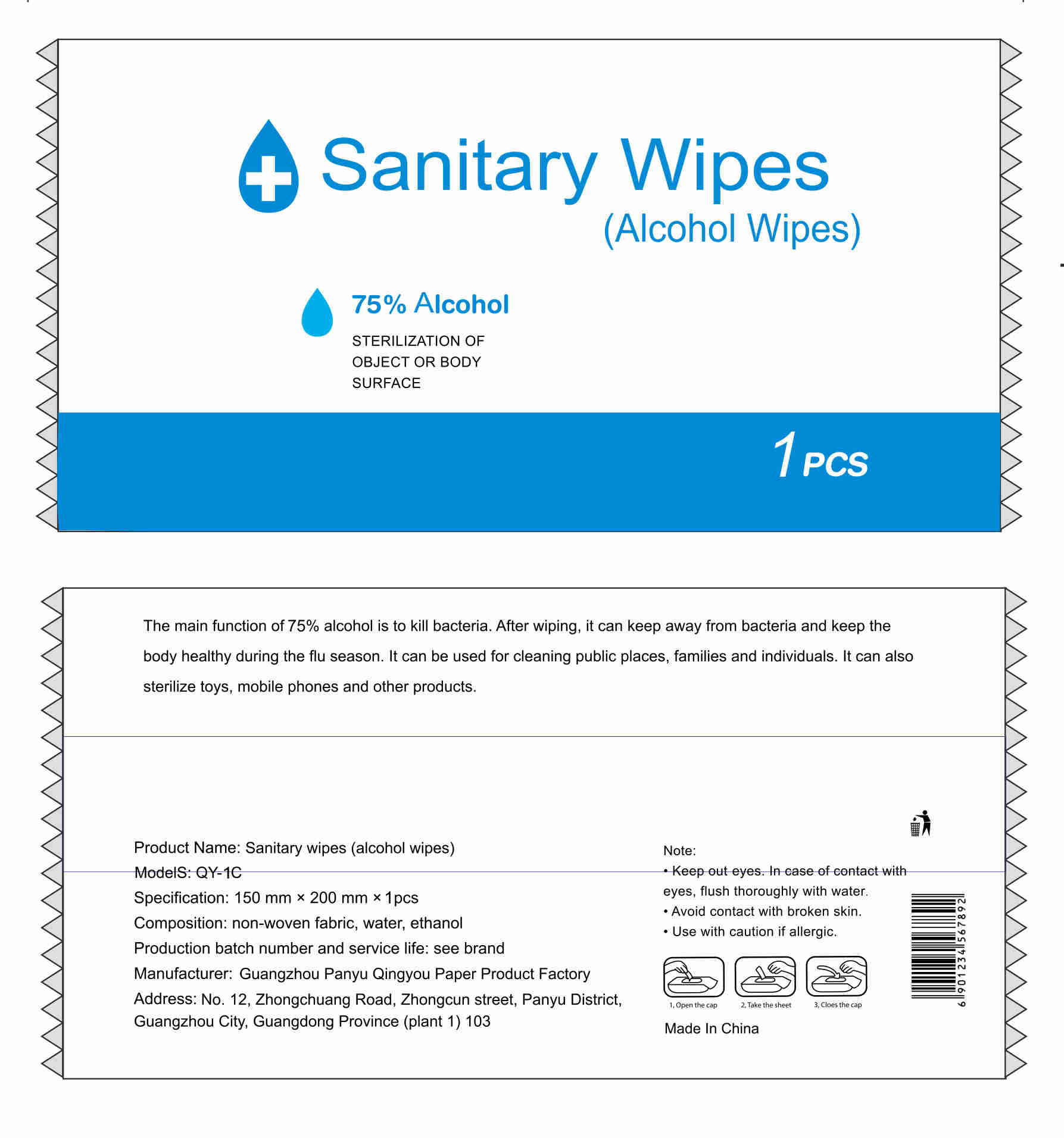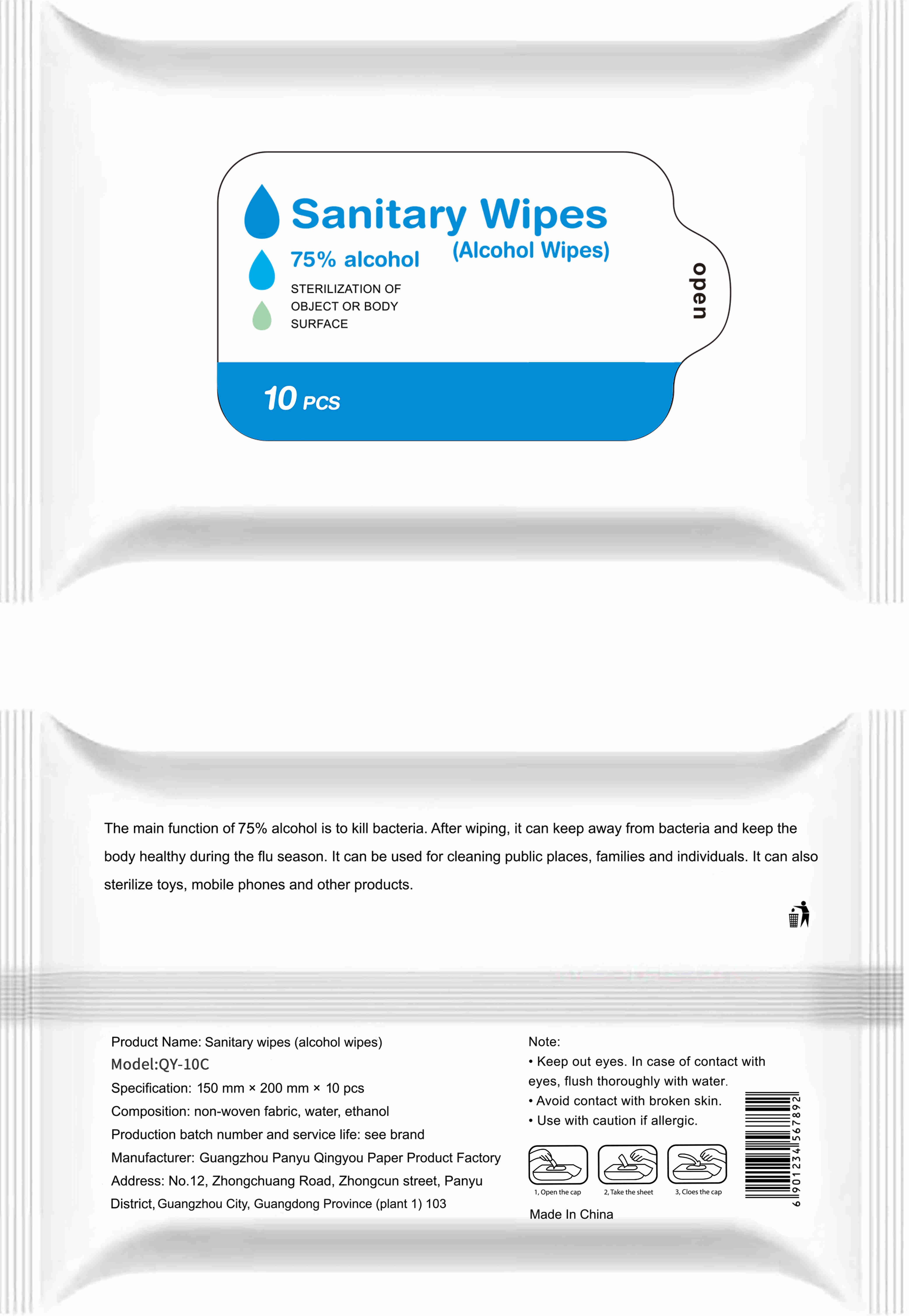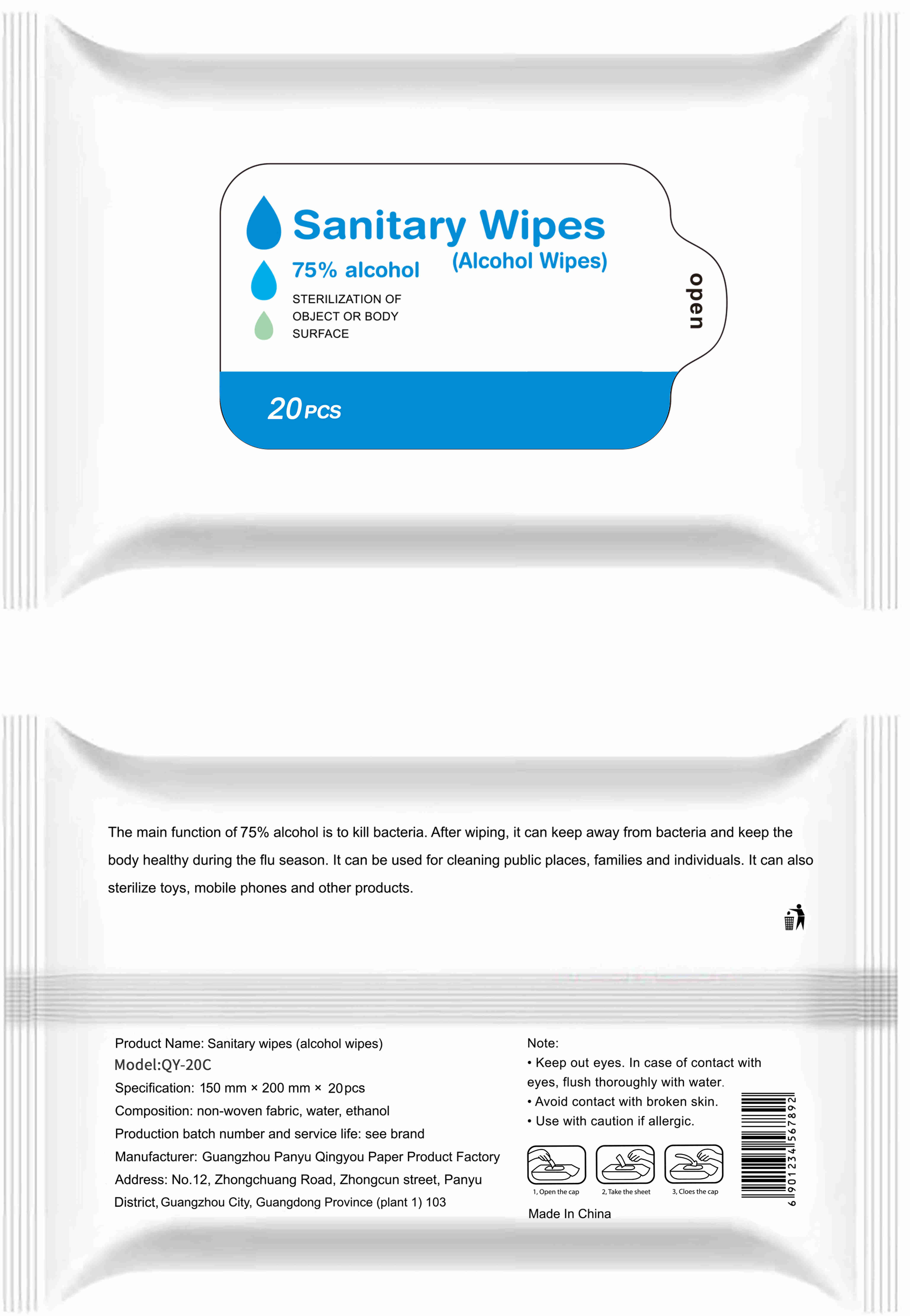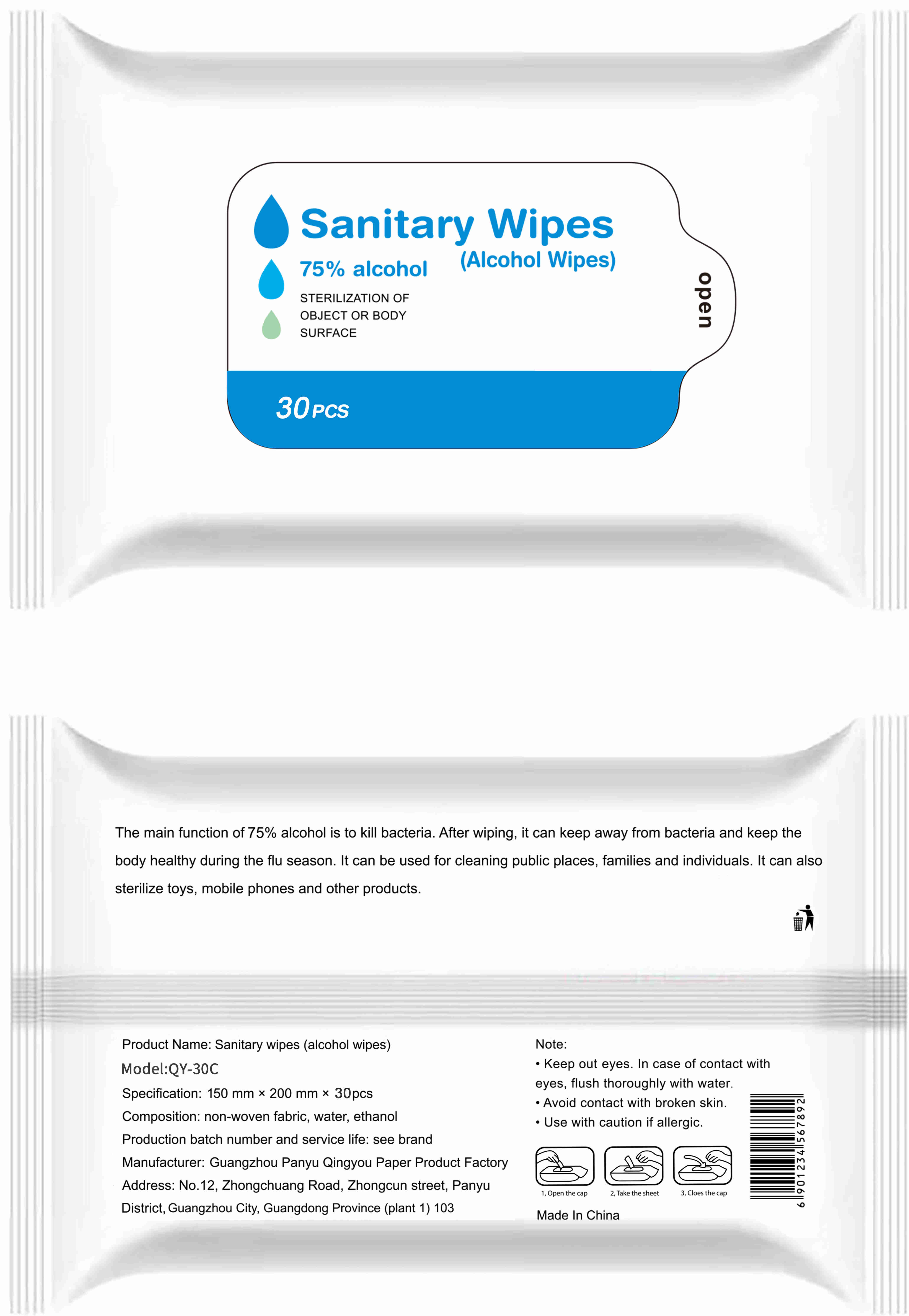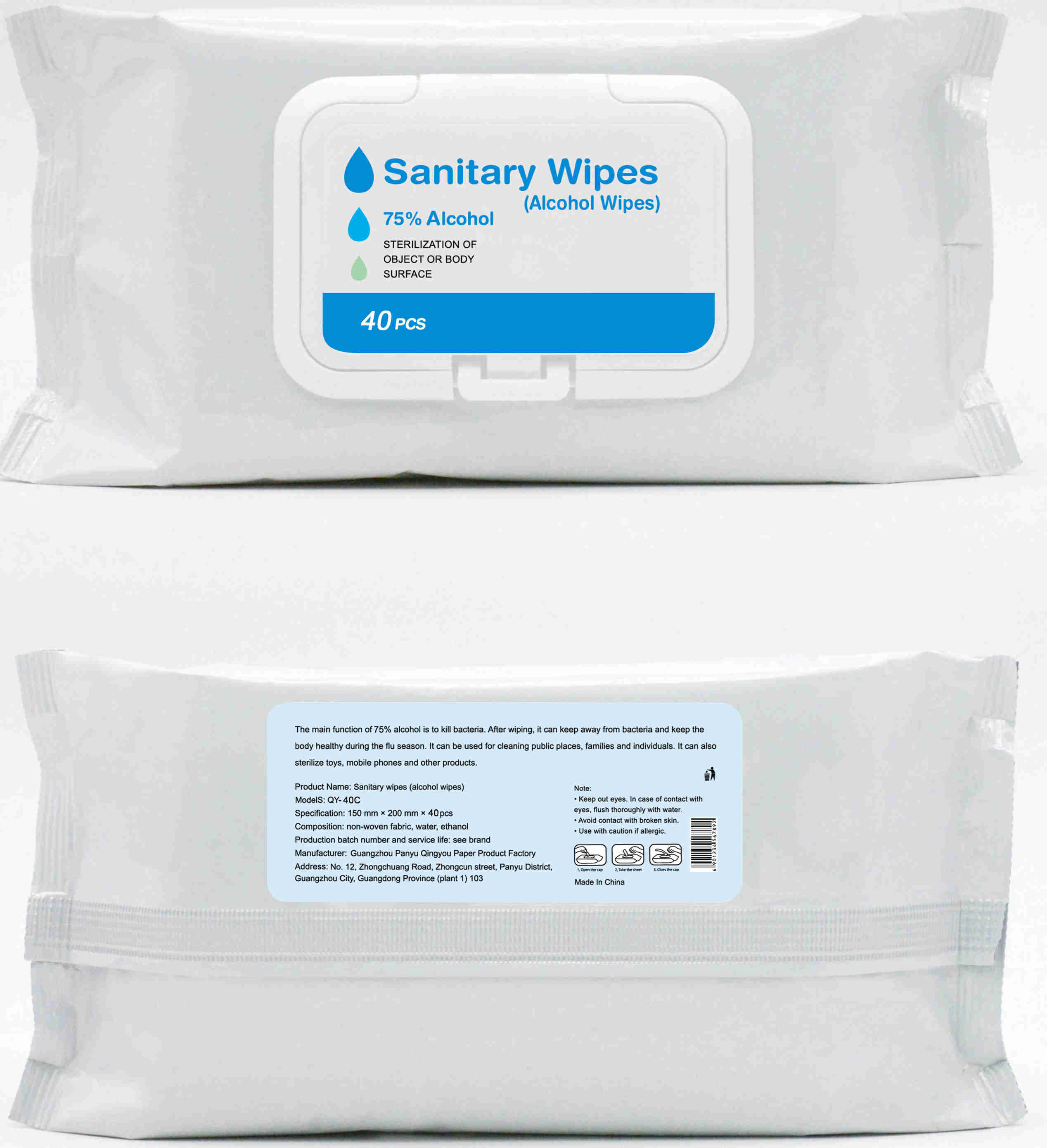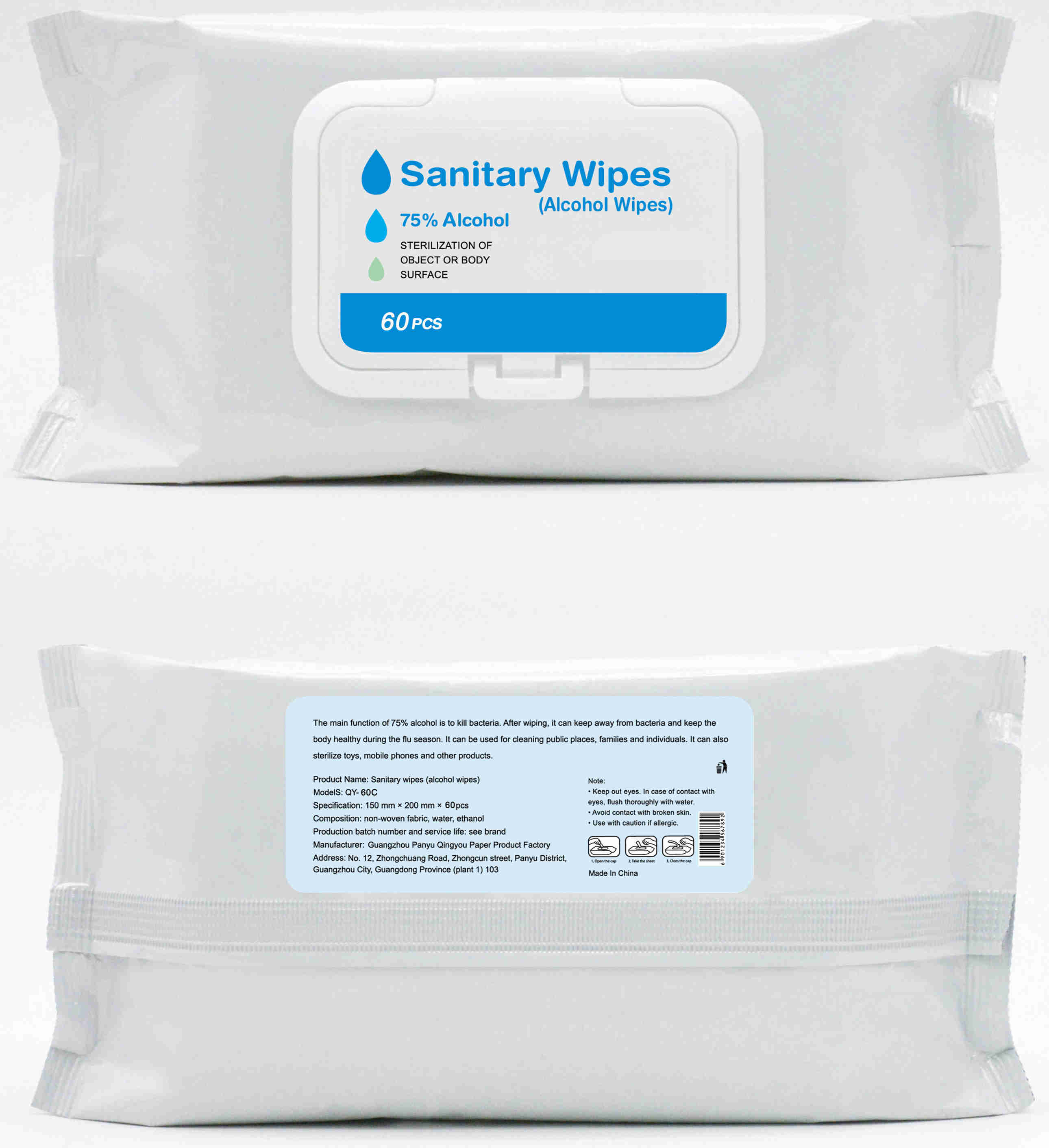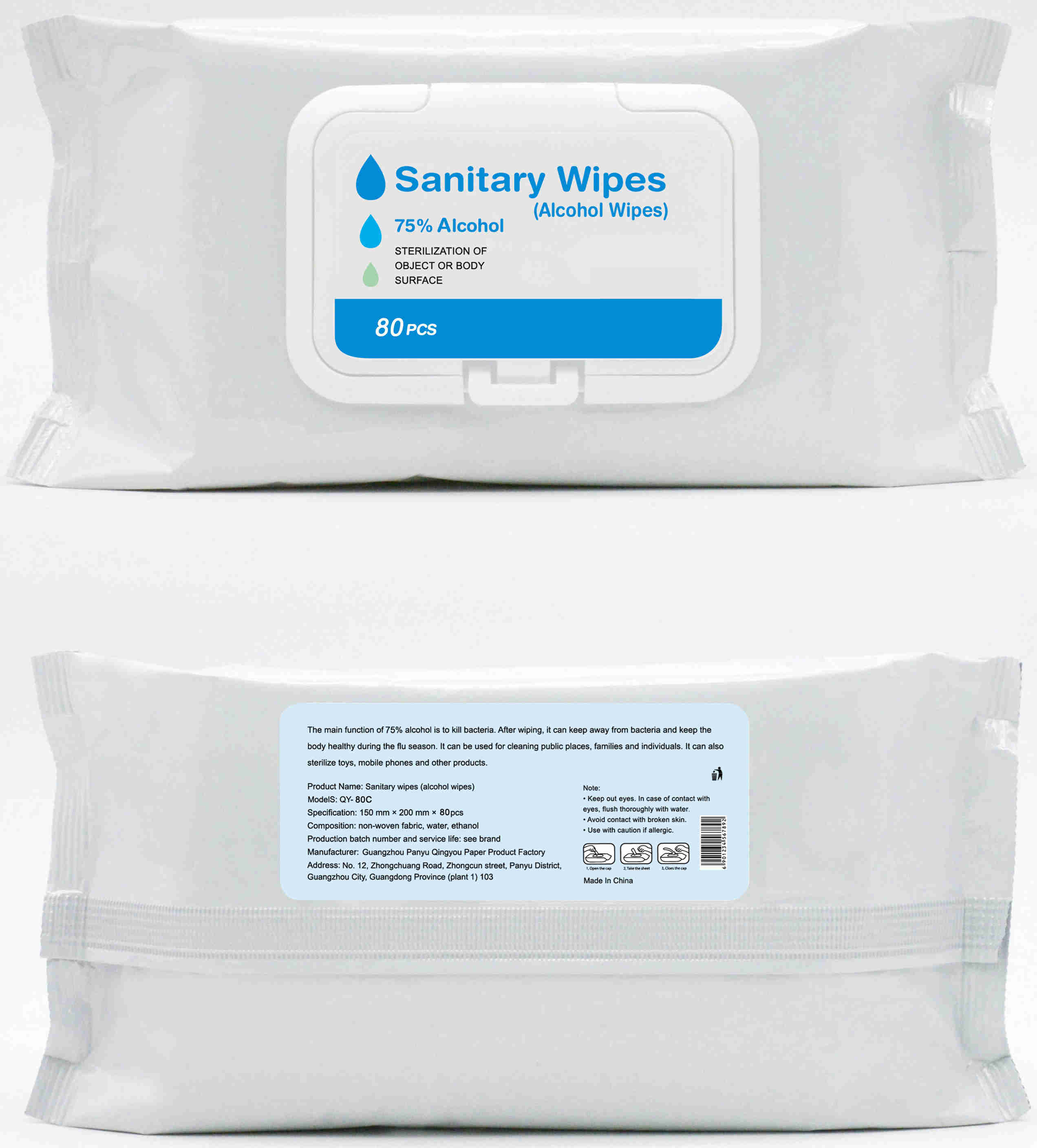 DRUG LABEL: Sanitary wipes(alcohol wipes)
NDC: 41853-002 | Form: CLOTH
Manufacturer: Guangzhou Panyu Qingyou Paper Product Factory
Category: otc | Type: HUMAN OTC DRUG LABEL
Date: 20200622

ACTIVE INGREDIENTS: ALCOHOL 270 mL/50 1
INACTIVE INGREDIENTS: WATER

DOSAGE AND ADMINISTRATION

Please do not place in direct sunlight or in a place with high temperature

INACTIVE INGREDIENT

water

INDICATIONS AND USAGE

1.Open the cap

2.Take the sheet

3.Close the cap

ACTIVE INGREDIENT

Ethanol

keep out of reach of children

PURPOSE

Disinfection
Sterilization
No Rinseing

WARNINGS

●Keep out eyes. In case of contact with eyes, flush thoroughly with water.
●Avoid contact with broken skin.
●Use with caution if allergic.